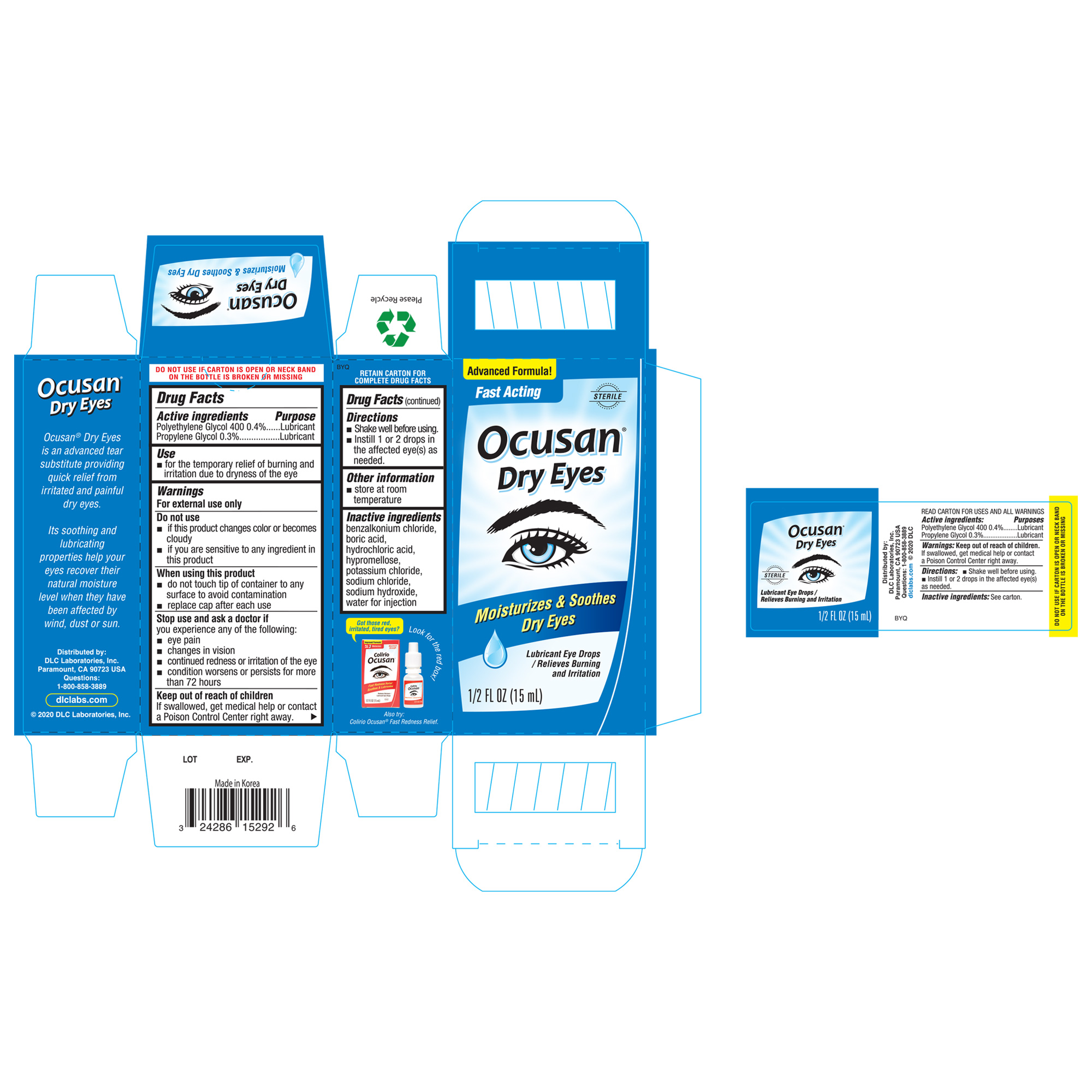 DRUG LABEL: Ocusan Dry Eyes
NDC: 24286-1292 | Form: LIQUID
Manufacturer: DLC Laboratories, Inc.
Category: otc | Type: HUMAN OTC DRUG LABEL
Date: 20250418

ACTIVE INGREDIENTS: PROPYLENE GLYCOL 3 mg/1 mL; POLYETHYLENE GLYCOL 400 4 mg/1 mL
INACTIVE INGREDIENTS: BORIC ACID; POTASSIUM CHLORIDE; HYDROCHLORIC ACID; BENZALKONIUM CHLORIDE; SODIUM CHLORIDE; WATER; SODIUM HYDROXIDE

Ocusan® Dry Eyes

Drug Facts

ACTIVE INGREDIENT

PURPOSE

Active ingredients | Purposes
Polyethylene Glycol 400 1% | Lubricant
proplyene Glycol | Lubricant

Use

- for the temporary relief of burning and irritation due to dryness of the eye

Warnings

For external use only

Do Not Use

- if this product changes color or becomes cloudy
- if you are sensitive to any ingredients in this product

When using this product

- do not touch tip of container to any surface to avoid contamination
- replace cap after each use

Stop use and ask a doctor if

you experience any of the following:

- eye pain
- changes in vision
- continued redness or irritation of the eye
- condition worsens or lasts more than 72 hours

Keep out of reach of children.If swallowed, get medical help or contact a Poison Control Center right away.

Directions

- shake well before using
- instill 1 to 2 drops in the affected eye(s) as needed

Other information

- store at room temperature

Inactive ingredients

benzalkonium chloride, boric acid, hydrochloric acid, hypromellose, potassium chloride, sodium chloride, sodium hydroxide, water for injection

Questions

1-800-858-3889

Distributed by:
DLC LABORATORIES, INC.
PARAMOUNT, CA 90723 USA

PRINCIPAL DISPLAY PANEL - 15 mL Bottle Box

Advanced Formula!

Fase Acting

Ocusan®

Dry Eyes
Moisturizes & Soothes Dry Eyes

Lubricant Eye Drops / Relieves Buring and Irritation

STERILE

1/2 FL OZ (15 mL)